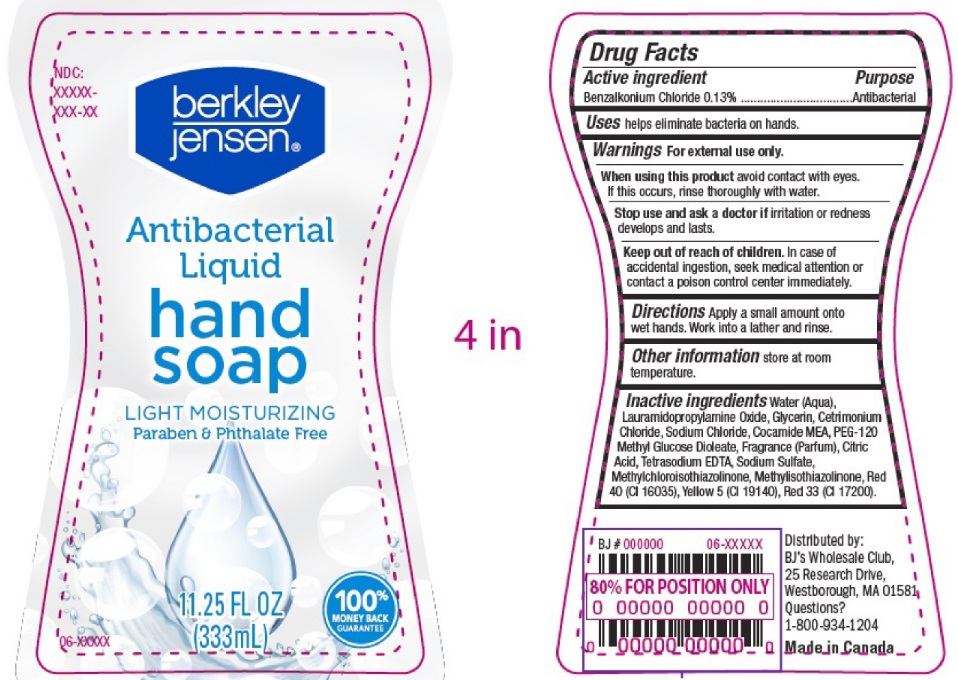 DRUG LABEL: berkley jensen
NDC: 63148-350 | Form: SOAP
Manufacturer: Apollo Health and Beauty Care
Category: otc | Type: HUMAN OTC DRUG LABEL
Date: 20241020

ACTIVE INGREDIENTS: BENZALKONIUM CHLORIDE 130 mg/100 mL
INACTIVE INGREDIENTS: SODIUM SULFATE; GLYCERIN; CETRIMONIUM CHLORIDE; SODIUM CHLORIDE; LAURAMIDOPROPYLAMINE OXIDE; METHYLCHLOROISOTHIAZOLINONE; WATER; METHYLISOTHIAZOLINONE; PEG-120 METHYL GLUCOSE DIOLEATE; FRAGRANCE CLEAN ORC0600327; CITRIC ACID MONOHYDRATE; EDETATE SODIUM; FD&C RED NO. 40; COCO MONOETHANOLAMIDE; BASIC YELLOW 5; D&C RED NO. 33

Berkley Jensen Antibacterial Liq Hand Soap, 63148-350-11

Active Ingredient.

Benzalkonium Chloride (0.13%)

Purpose

Antibacterial

Uses

Helps eliminate bacteria on hands.

Warnings

For external use only

When using this product

Avoid contact with eyes. If this occurs, rinse thoroughly with water.

Stop use and ask a doctor if

irritation or redness develops and lasts

Keep out of reach of children.

In case of accidental ingestion, seek medical attention or contact a poison center immediately.

Directions

- Apply a small amount onto wet hands
- Work into a lather and rinse

Other Information

Store at room temperature

Inactive Ingredients

Water (Aqua), Lauramidopropylamide Oxide, Glycerin, Cetrimonium Chloride, Sodium Chloride, Cocamide MEA, PEG – 120 Methyl Glucose Dioleate, Fragrance (Parfum), Citric Acid, Tetrasodium EDTA, Sodium Sulfate, Methylchloroisothiazolinone, Methylisothiazolinone, Red 40 (CI 16035), Yellow 5 (CI 19140), Red 33 (CI 17200),